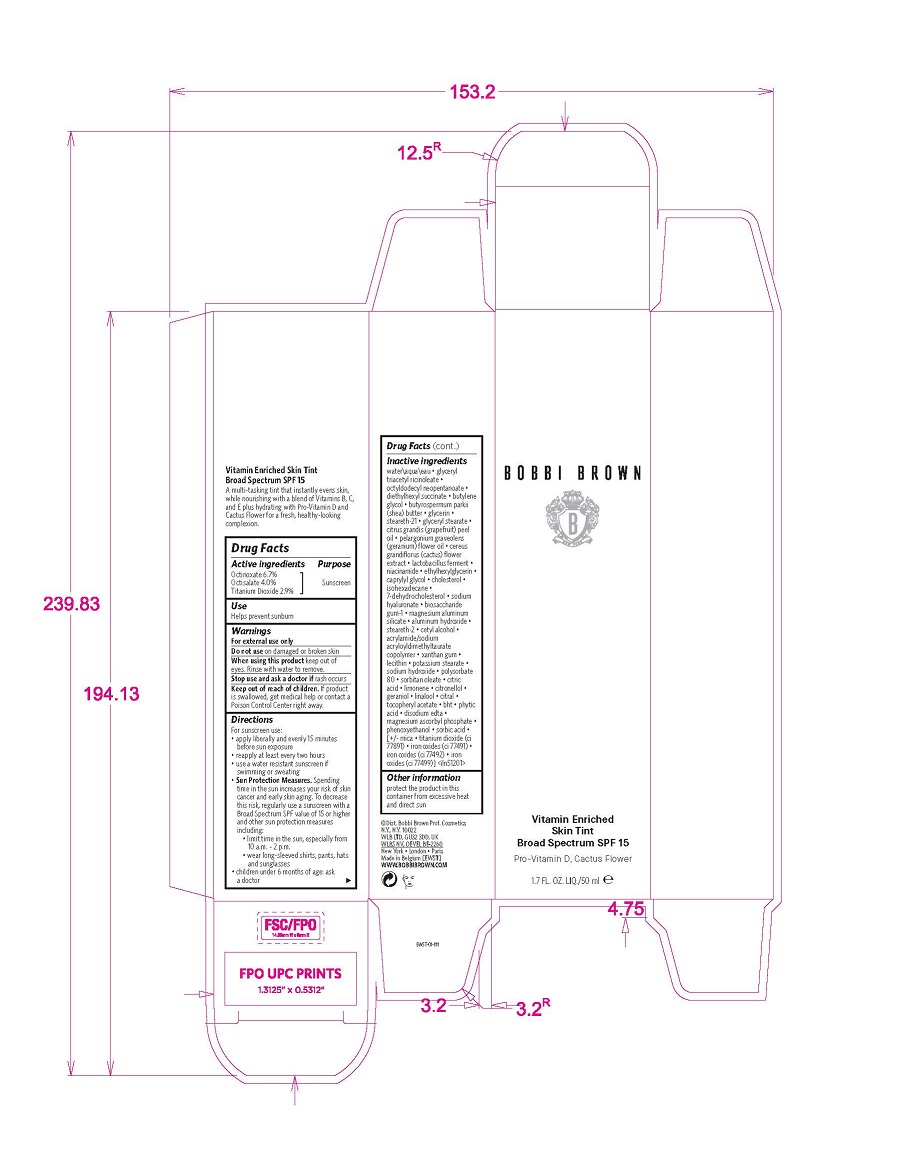 DRUG LABEL: VITAMIN ENRICHED SKIN TINT BROAD SPECTRUM SPF 15
NDC: 64141-033 | Form: LIQUID
Manufacturer: Bobbi Brown Professional Cosmetics Inc.
Category: otc | Type: HUMAN OTC DRUG LABEL
Date: 20241122

ACTIVE INGREDIENTS: OCTINOXATE 67 mg/1 mL; OCTISALATE 40 mg/1 mL; TITANIUM DIOXIDE 29 mg/1 mL
INACTIVE INGREDIENTS: ETHYLHEXYLGLYCERIN; ISOHEXADECANE; HYALURONATE SODIUM; POTASSIUM STEARATE; .BETA.-CITRONELLOL, (R)-; FERRIC OXIDE YELLOW; LECITHIN, SOYBEAN; POLYSORBATE 80; GLYCERYL TRIACETYL RICINOLEATE; SHEA BUTTER; GLYCERIN; LIMOSILACTOBACILLUS FERMENTUM; NIACINAMIDE; CAPRYLYL GLYCOL; CHOLESTEROL; CITRIC ACID MONOHYDRATE; DIETHYLHEXYL SUCCINATE; GLYCERYL MONOSTEARATE; SELENICEREUS GRANDIFLORUS FLOWER; LIMONENE, (+)-; GERANIOL; LINALOOL, (+/-)-; CITRAL; ALPHA-TOCOPHEROL ACETATE; FYTIC ACID; MAGNESIUM ASCORBYL PHOSPHATE; PHENOXYETHANOL; SORBIC ACID; FERRIC OXIDE RED; FERROSOFERRIC OXIDE; CETYL ALCOHOL; XANTHAN GUM; SODIUM HYDROXIDE; 7-DEHYDROCHOLESTEROL; BIOSACCHARIDE GUM-1; MAGNESIUM ALUMINUM SILICATE; ALUMINUM HYDROXIDE; BUTYLENE GLYCOL; STEARETH-21; CITRUS MAXIMA FRUIT RIND OIL; PELARGONIUM GRAVEOLENS FLOWER OIL; OCTYLDODECYL NEOPENTANOATE; WATER; STEARETH-2; SORBITAN MONOOLEATE; BUTYLATED HYDROXYTOLUENE; EDETATE DISODIUM ANHYDROUS; MICA; SODIUM ACRYLOYLDIMETHYLTAURATE-ACRYLAMIDE COPOLYMER (1:1; 90000-150000 MPA.S)

VITAMIN ENRICHED SKIN TINT BROAD SPECTRUM SPF 15

Active ingredients

Octinoxate 6.7%
Octisalate 4.0%
Titanium Dioxide 2.9%

Purpose

Sunscreen

Use

Helps prevent sunburn

Warnings

Do not use on damaged or broken skin

When using this product keep out of eyes. Rinse with water to remove.

Stop use and ask a doc tor if rash occurs

Keep out of reach of children. If product is swallowed, get medical help or contact a Poison Control Center right away.

Directions

For sunscreen use:
• apply liberally and evenly 15 minutes
before sun exposure
• reapply at least every two hours
• use a water resistant sunscreen if
swimming or sweating

Sun Protection Measures. Spending
time in the sun increases your risk of skin
cancer and early skin aging. To decrease
this risk, regularly use a sunscreen with a
Broad Spectrum SPF value of 15 or higher
and other sun protection measures
including:
• limit time in the sun, especially fr om
10 a.m. – 2 p.m.
• wear long-sleeved shirts, pants, hats
and sunglasses
• children under 6 months of age: ask
a doctor

Inactive ingredients

water\aqua\eau • glyceryl
triacetyl ricinoleate •
octyldodecyl neopentanoate •
diethylhexyl succinate • butylene
glycol • butyrospermum parkii
(shea) butter • glycerin •
steareth-21 • glyceryl stearate •
citrus grandis (grapefruit) peel
oil • pelargonium graveolens
(geranium) flower oil • cereus
grandiflorus (cactus) flower
extract • lactobacillus ferment •
niacinamide • ethylhexylglycerin •
caprylyl glycol • cholesterol •
isohexadecane •
7-dehydrocholesterol • sodium
hyaluronate • biosaccharide
gum-1 • magnesium aluminum
silicate • aluminum hydroxide •
steareth-2 • cetyl alcohol •
acrylamide/sodium
acryloyldimethyltaurate
copolymer • xanthan gum •
lecithin • potassium stearate •
sodium hydroxide • polysorbate
80 • sorbitan oleate • citric
acid • limonene • citronellol •
geraniol • linalool • citral •
tocopheryl acetate • bht • phytic
acid • disodium edta •
magnesium ascorbyl phosphate •
phenoxyethanol • sorbic acid •
[+/- mica • titanium dioxide (ci
77891) • iron oxides (ci 77491) •
iron oxides (ci 77492) • iron
oxides (ci 77499)]

Other Information

protect the product in this container from excessive heat and direct sun

PACKAGE LABEL

BOBBI BROWN

Vitamin Enriched
Skin Tint
Broad Spectrum SPF 15

Pro-Vitamin D, Cactus Flower

1.7 FL. OZ. LIQ./50 ml e